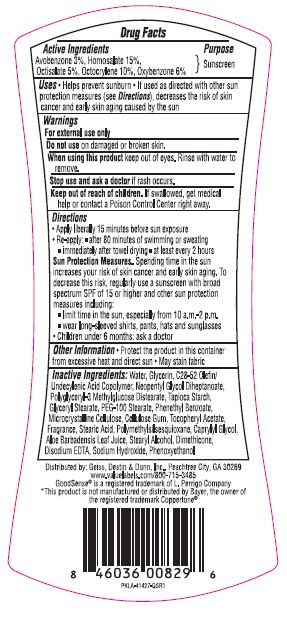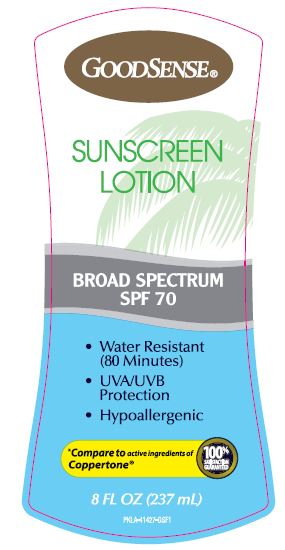 DRUG LABEL: GoodSense Sunscreen SPF 70
NDC: 70281-661 | Form: LOTION
Manufacturer: Solskyn Personal Care LLC
Category: otc | Type: HUMAN OTC DRUG LABEL
Date: 20190724

ACTIVE INGREDIENTS: HOMOSALATE 15 g/100 g; OXYBENZONE 6 g/100 g; AVOBENZONE 3 g/100 g; OCTISALATE 5 g/100 g; OCTOCRYLENE 10 g/100 g
INACTIVE INGREDIENTS: EDETATE DISODIUM ANHYDROUS; PHENOXYETHANOL; POLYMETHYLSILSESQUIOXANE (4.5 MICRONS); SODIUM HYDROXIDE; WATER; GLYCERIN; UNDECYLENIC ACID; NEOPENTYL GLYCOL DIHEPTANOATE; POLYGLYCERYL-3 DIISOSTEARATE; STARCH, TAPIOCA; GLYCERYL STEARATE/PEG-100 STEARATE; PHENETHYL BENZOATE; MICROCRYSTALLINE CELLULOSE; CARBOXYMETHYLCELLULOSE SODIUM, UNSPECIFIED FORM; .ALPHA.-TOCOPHEROL ACETATE; STEARIC ACID; CAPRYLYL GLYCOL; ALOE VERA LEAF; DIMETHICONE

GoodSense Sunscreen Lotion SPF 70

Active Ingredients

Avobenzone 3%, Homosalate 15%, Octisalate 5%

Octocrylene 10%, Oxybenzone 6%

Purpose

Sunscreen

Uses

Helps prevent sunburn.
If used as directed with other sun protection measures (see Directions), decreases the risk of skin cancer and early skin aging caused by the sun

Warnings

For external use only

Do not use on damaged or broken skin

When using this product keep out of eyes. Rinse with water to remove.

Stop use and ask a doctor if rash occurs.

Keep out of reach of children. If swallowed, get medical help or contact a Poison Control Center right away.

Directions

Apply liberally 15 minutes before sun exposure
Re-apply after 80- minutes of swimming or sweating

- Immediately after towel drying
- At least every 2 hours

Sun Protection Measures. Spending time in the sun increases your risk of skin cancer and early skin aging. To decrease this risk, regularly use a sunscreen with broad spectrum SPF of 15 or high and other sun protection measures including:

- Limit time in the sun, especially from 10a.m.-2 p.m.
- Wear long-sleeved shirts, pants, hats, and sunglasses.
- Children under 6 months: ask a doctor

Other Information

- Protect the product in this container from excessive heat and direct sun
- May stain fabric

Inactive Ingredients

Water, Glycerin, C28-52 Olefin/Undecylenic Acid Copolymer, Neopentyl Glycol Diheptanoate, Polyglyceryl -3 Methylglucose Distearate, Tapioca Starch, Glyceryl Stearate, PEG-I00 Stearate, Phenethyl Benzoate, Microcrystalline Cellulose, Cellulose Gum, Tocopheryl Acetate, Fragrance, Stearic Acid, Polymethylsilsesquioxane, Caprylyl Glycol, Aloe Barbadensis Leaf Juice, Stearyl Alcohol, Dimethicone, Disodium EDTA, Sodium Hydroxide, Phenoxyethanol

Questions

Distributed by Geiss, Destin, & Dunn Inc., Peach tree City, GA 30269

www.valuelabels.com /800-715-3485

*GoodSense® is a registered trademark of L. Perrigo Company *This product is not manufactured or distributed by Bayer, the owner of the registered trademark Coppertone®

Principal Display Panel

GOODSENSE

SUNSCREEN LOTION

BROAD SPECTRUM

SPF 70

- Water Resistant (80 Minutes)
- UVA/UVB Protection
- Hypoallergenic

Compare to active ingredients of Coppertone

100% Satisfaction Guaranteed

8 FL OZ (237 mL)